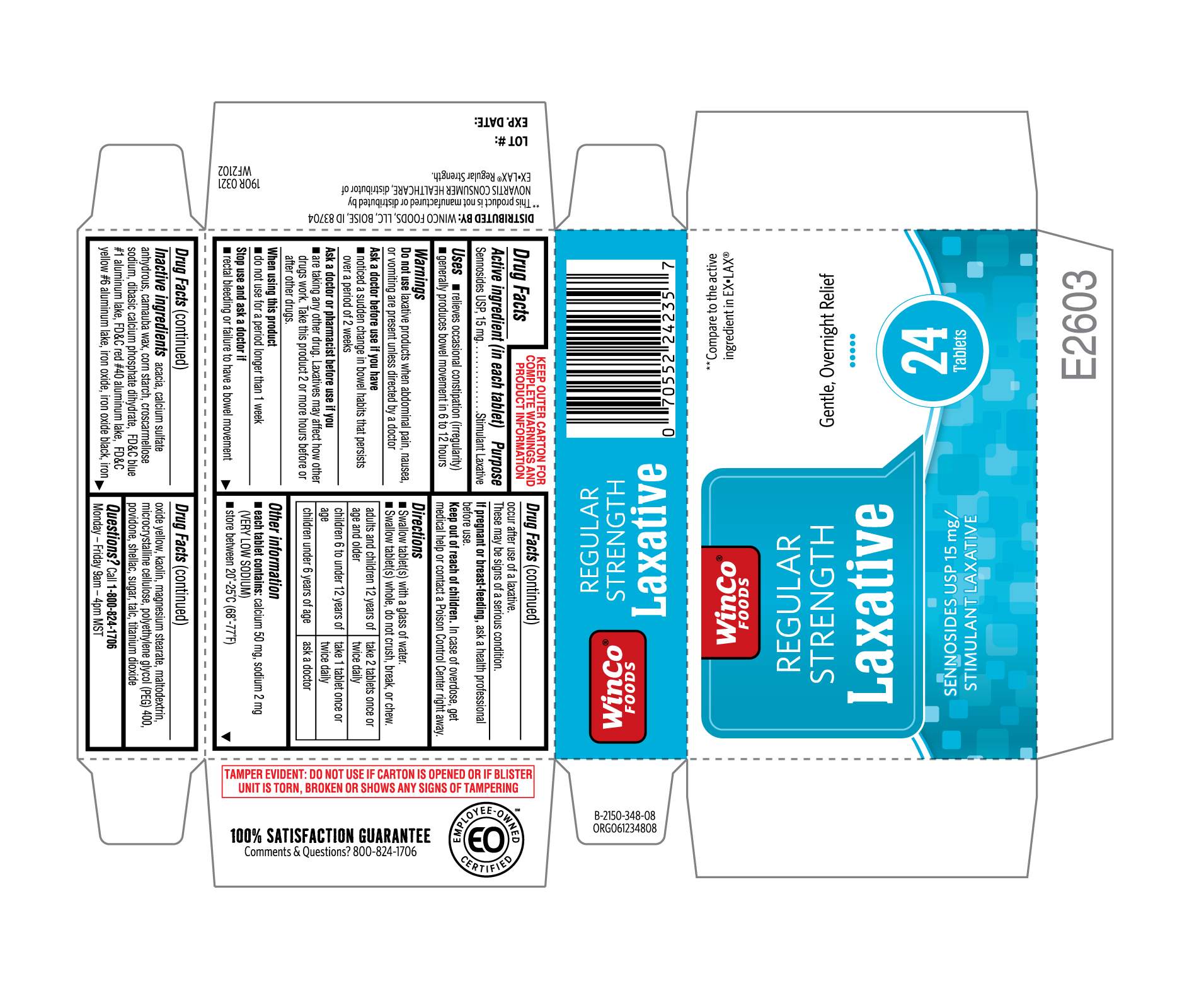 DRUG LABEL: Regular Strength Laxative
NDC: 67091-384 | Form: TABLET
Manufacturer: WinCo Foods LLC
Category: otc | Type: HUMAN OTC DRUG LABEL
Date: 20220108

ACTIVE INGREDIENTS: SENNOSIDES 15 mg/1 1
INACTIVE INGREDIENTS: POLYETHYLENE GLYCOL 400; SHELLAC; TITANIUM DIOXIDE; CALCIUM SULFATE ANHYDROUS; CARNAUBA WAX; STARCH, CORN; MALTODEXTRIN; RAW SUGAR; ACACIA; KAOLIN; TALC; FERROSOFERRIC OXIDE; MAGNESIUM STEARATE; DIBASIC CALCIUM PHOSPHATE DIHYDRATE; FD&C BLUE NO. 1 ALUMINUM LAKE; FD&C YELLOW NO. 6; CROSCARMELLOSE SODIUM; FERRIC OXIDE YELLOW; CELLULOSE, MICROCRYSTALLINE; FD&C RED NO. 40

190R Winco Foods 67091 384 Sennosides USP 15 mg 24ct

Active ingredient (in each tablet)

Sennosides USP, 15 mg

Purpose

Stimulant Laxative

Uses
• relieves occasional constipation (irregularity)
• generally produces bowel movement in 6 to12 hours

Warnings

Do not use laxative products when abdominal pain, nausea, or vomiting are present unless directed by a doctor

Ask a doctor before use if you have

- noticed a sudden change in bowel habits that persists over a period of 2 weeks

Ask a doctor or pharmacist before use if you

- are taking any other drug. Laxatives may affect how other drugs work. Take this product 2 or more hours before or after other drugs.

When using this product

- do not use for a period longer than 1 week

Stop use and ask a doctor if

- rectal bleeding or failure to have a bowel movement occur after use of a laxative.

These may be signs of a serious condition.

PREGNANCY OR BREAST FEEDING

If pregnant or breast-feeding, ask a health professional before use.

Keep out of reach of children. In case of overdose, get medical help or contact a Poison Control Center right away.

Directions

• Swallow tablet(s) with a glass of water
• Swallow tablet(s) whole, do not crush, break, or chew.

adults and children 12 years of age and older | take 2 tablets once or twice daily
children 6 to under 12 years of age | take 1 tablet once or twice daily
children under 6 years of age | ask a doctor

Other information
• each tablet contains: calcium 50 mg, sodium 2 mg (VERY LOW SODIUM)
• store between 20°-25°C (68°-77°F)

Inactive ingredient acacia, calcium sulfate anhydrous, carnauba wax, corn starch, croscarmellose sodium, dibasic calcium phosphate dihydrate, FD&C blue #1 aluminum lake, FD&C red #40 aluminum lake, FD&C yellow #6 aluminum lake, iron oxide, iron oxide black, iron oxide yellow, kaolin, magnesium stearate, maltodextrin, microcrystalline cellulose, polyethylene glycol (PEG) 400, povidone, shellac, sugar, talc, titanium dioxide

Questions? Call 1-800-824-1706
Monday – Friday 9am – 4pm MST